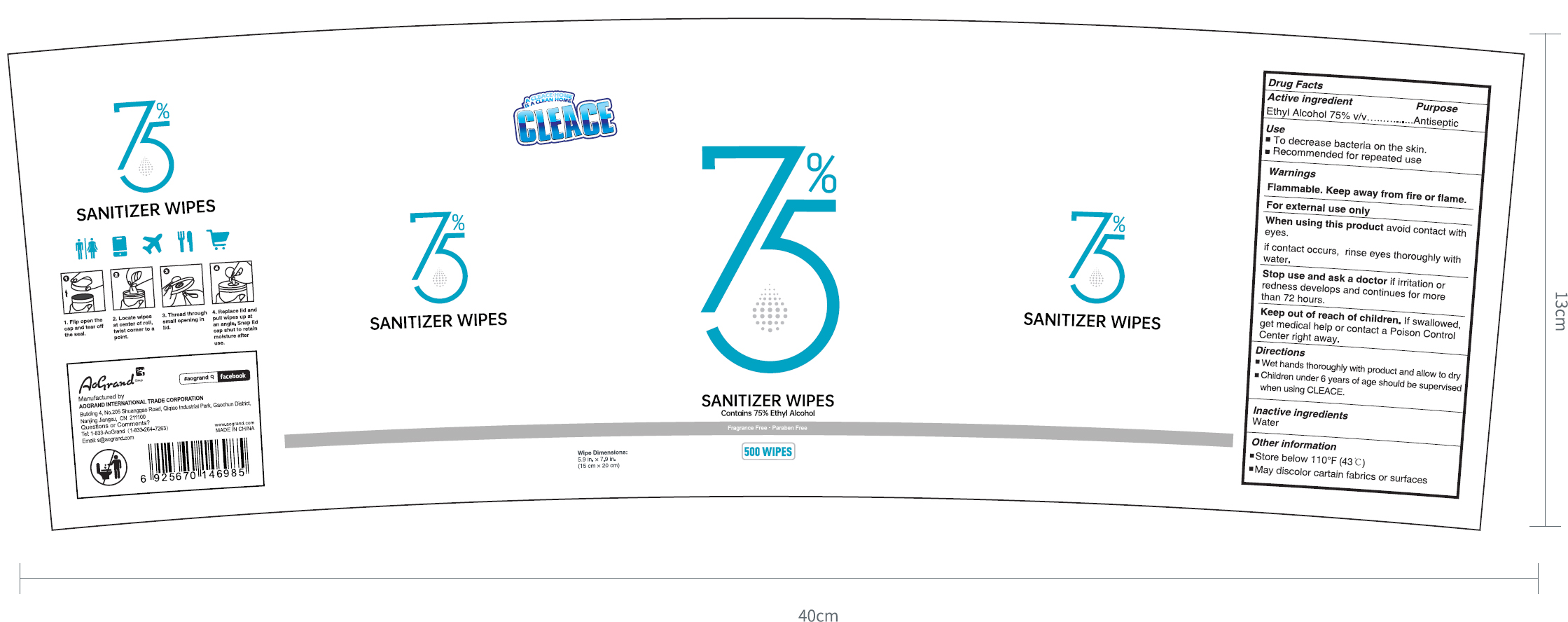 DRUG LABEL: CLEACE 75% Ethyl Alcohol Sanitizer Wipes
NDC: 74621-022 | Form: CLOTH
Manufacturer: Aogrand International Trade Corporation
Category: otc | Type: HUMAN OTC DRUG LABEL
Date: 20230211

ACTIVE INGREDIENTS: ALCOHOL 75 mL/100 g
INACTIVE INGREDIENTS: WATER

CLEACE 75% Ethyl Alcohol Sanitizer Wipes (500 wipes)

Active Ingredient

Ethyl Alcohol 75% v/v. Purpose: Antiseptic

Purpose

Antiseptic

Use

- To decrease bacteria on the skin.
- Recommended for repeated use

Warnings

For external use only.

Flammable. Keep away from fire or flame.

When using this product

avoid contact with eyes.

If contact occurs, rinses eyes thoroughly with water.

Stop use and ask a doctor if

irritation or redness develops and continues for more than 72 hours.

Keep out of reach of children.

If swallowed, get medical help or contact a poison control center right away.

Directions

- Wet hands thoroughly with product and allow to dry
- Children under 6 years of age should be supervised when using CLEACE.

Inactive ingredients

Water

Other information

- Store below 110F (43C)
- May discolor certain fabrics or surfaces

Package Label - Principal Display Panel

500PCS NDC: 74621-022-01

A CLEACE HOME

IS A CLEAN HOME

CLEACE

75%

Sanitizer wipes

Contains 75% Ethyl Alcohol

Fragrance Free

Paraben Free

Wipe Dimensions

5.9 in x 7.9 in

(15 cm x 20 cm)

500 WIPES